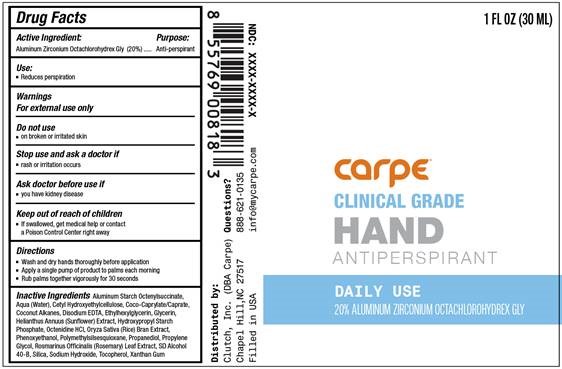 DRUG LABEL: Hand Antiperspirant Daily Use
NDC: 74307-007 | Form: CREAM
Manufacturer: Clutch Inc
Category: otc | Type: HUMAN OTC DRUG LABEL
Date: 20260226

ACTIVE INGREDIENTS: ALUMINUM ZIRCONIUM OCTACHLOROHYDREX GLY 20 g/100 mL
INACTIVE INGREDIENTS: ALUMINUM STARCH OCTENYLSUCCINATE; CETYL HYDROXYETHYLCELLULOSE (350000 MW); COCONUT ALKANES; ETHYLHEXYLGLYCERIN; PROPYLENE GLYCOL; PHENOXYETHANOL; POLYMETHYLSILSESQUIOXANE (4.5 MICRONS); XANTHAN GUM; PROPANEDIOL; OCTENIDINE HYDROCHLORIDE; RICE BRAN; SODIUM HYDROXIDE; ROSEMARY; TOCOPHEROL; GLYCERIN; HELIANTHUS ANNUUS FLOWERING TOP; COCOYL CAPRYLOCAPRATE; WATER; EDETATE DISODIUM; SILICON DIOXIDE

HAND ANTIPERSPIRANT DAILY USE

Active Ingredient Purpose

Aluminum Zirconium Tetrachlorohydrex Gly (20%) Antiperspirant

Use

reduces perspiration

KEEP OUT OF REACH OF CHILDREN

Keep out reach of children.If swallowed get medical help or contact a Poison Control Center right away

INDICATIONS AND USAGE

Stop useif rash or irritation occurs

Warnings

For external use only.

Do not useon broken or irritated skin

Ask a doctor before use ifyou have kidney disease.

Directions

- wash and dry hands thoroughly before application
- Apply a single pump of product to palms each morning
- Rub Balms together vigorously for 30 seconds

INACTIVE INGREDIENT

Inactive IngredientsAluminum Starch Octenylsuccinate, Aqua (water), Cetyl Hydroxyethylcellulose, Coco-Caprylate/Caprate.Coconut Alkanes, Disodium EDTA, Ethylhexylglycerin, Glycerin, Helianthus Annuus (Suflower) Extract, Hydroxypropyl Starch Phosphate, Octenidine HCL, Oryza SAtiva (Rice) Bran Extract, Phenoxyethanol, Polymethylsilsesquioxane, Propanediol, Propylene Glycol, Rosmarinus Officinalis (Rosemary) Leaf Extract, SD Alcohol 40-B, SIlica, Sodium Hydroxide, Tocopherol, Xanthan Gum

PACKAGE LABEL

Carpe

Clinical Grade HAND

Antiperspirant

Daily Use

20% Aluminum Zirconium Octachlorohydrex GLY